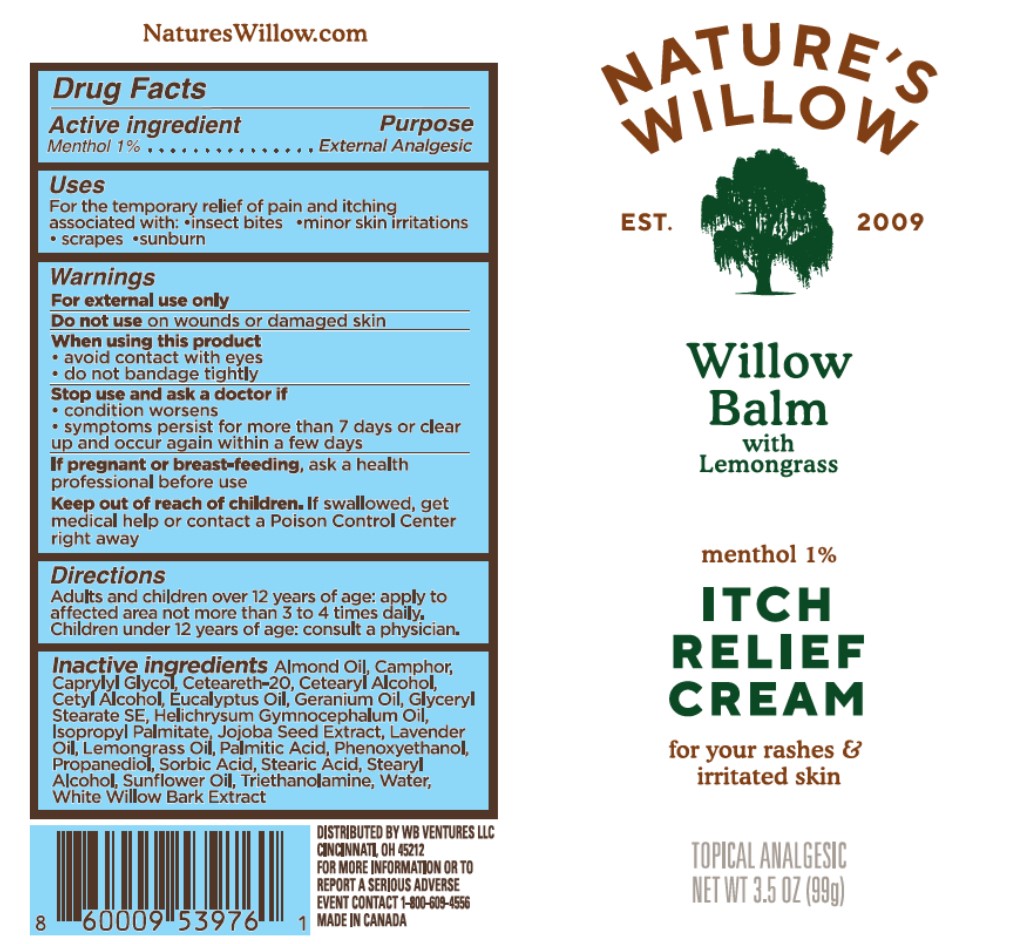 DRUG LABEL: Natures Willow Balm Itch Relief Cream
NDC: 73498-028 | Form: CREAM
Manufacturer: WB Ventures LLC
Category: otc | Type: HUMAN OTC DRUG LABEL
Date: 20231219

ACTIVE INGREDIENTS: MENTHOL 10 mg/1 g
INACTIVE INGREDIENTS: PELARGONIUM GRAVEOLENS FLOWER OIL; SIMMONDSIA CHINENSIS SEED; EUCALYPTUS OIL; CETYL ALCOHOL; CAMPHOR (SYNTHETIC); STEARYL ALCOHOL; LAVENDER OIL; TROLAMINE; CETOSTEARYL ALCOHOL; HELICHRYSUM GYMNOCEPHALUM WHOLE; GLYCERYL STEARATE SE; WEST INDIAN LEMONGRASS OIL; CAPRYLYL GLYCOL; SORBIC ACID; SUNFLOWER OIL; PHENOXYETHANOL; POLYOXYL 20 CETOSTEARYL ETHER; STEARIC ACID; PROPANEDIOL; ISOPROPYL PALMITATE; SALIX ALBA BARK; PALMITIC ACID; WATER; ALMOND OIL

Natures Willow Balm Itch Relief Cream

Active Ingredient

Menthol 1%

Purpose

External Analgesic

Uses

For the temporary relief of pain and itching associated with:

- insect bites

- minor skin irritations

- scrapes

- sunburn

Warnings

For External use only

Do not use on wounds or damaged skin

When using this product

- avoid contact wth eyes
- do not bandage tightly

Stop use and ask a dctor if

- condition worsen
- symptoms persist for more than 7 days sor clear up and occur again wthin a few days

If pregnant or breast-feeding, ask a health professional before use

Keep out of reach of children, if swallowed, get medical help or contact a Poison Control Center right away

Directions

Adults and children over 2 years of age: apply to affected area not more than 3 to 4 times daily

Children under 2 years of age: consult a physician

Inactive Ingredients

Almond Oil, Camphor, Caprylyl Glycol, Ceteareth-20, Cetearyl Alcohol, Cetyl Alcohol, Eucalyptus Oil, Geranium Oil, Glyceryl Stearate SE, Helichrysum Gymnocephalum Oil, Isopropyl Palmitate, Jojoba Seed Extract, Lavender Oil, Lemongrass Oil, Palmitic Acid, Phenoxyethanol, Propanediol, Sorbic Acid, Stearic Acid, Stearyl Alcohol, Sunflower Oil, Triethanolamine, Water, White Willow Bark Extract

Distributed by WB Ventures LLC, Cincinnati, OH 45212

For more information or to report a serious adverse event contact 1-888-609-4556